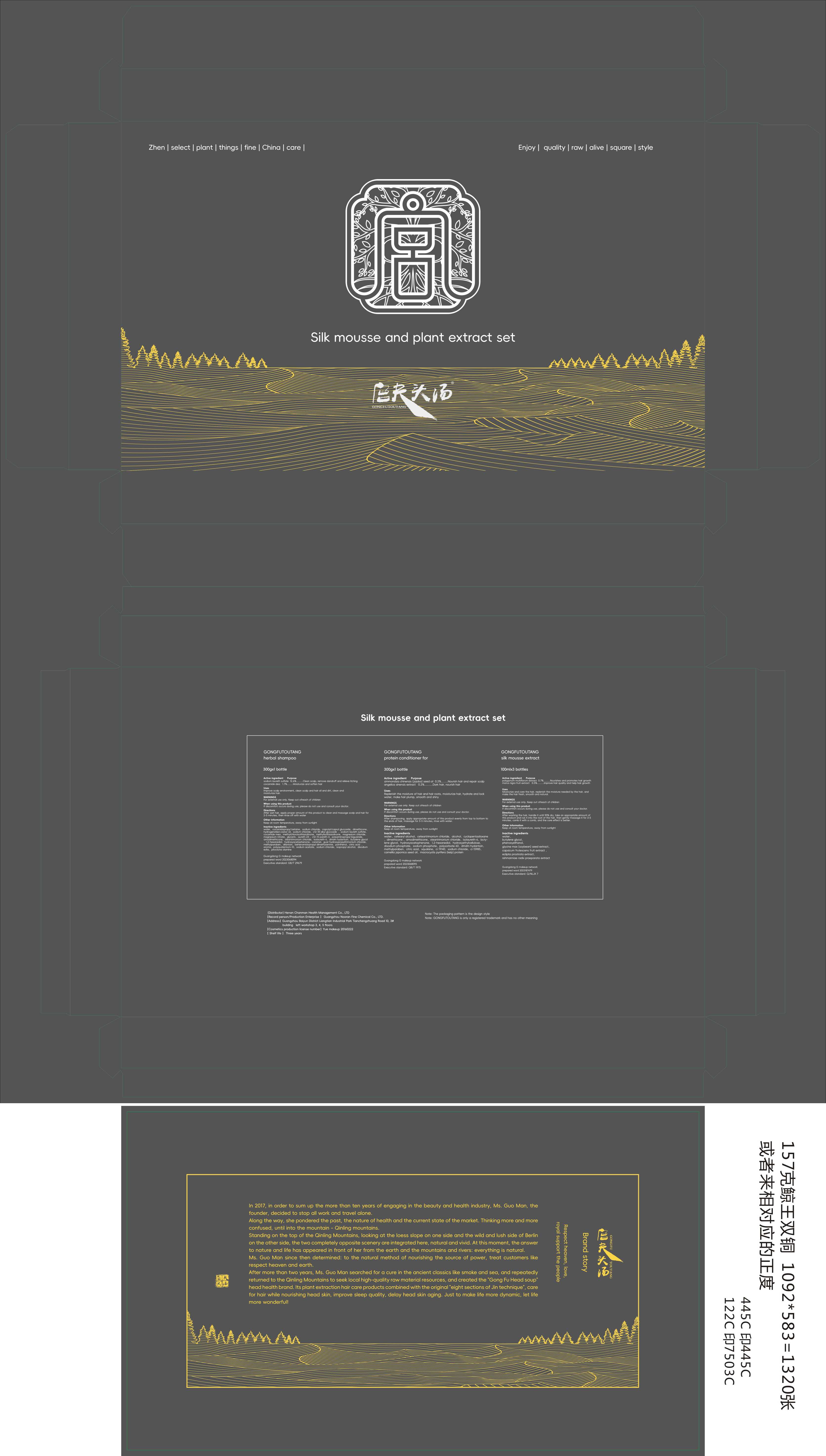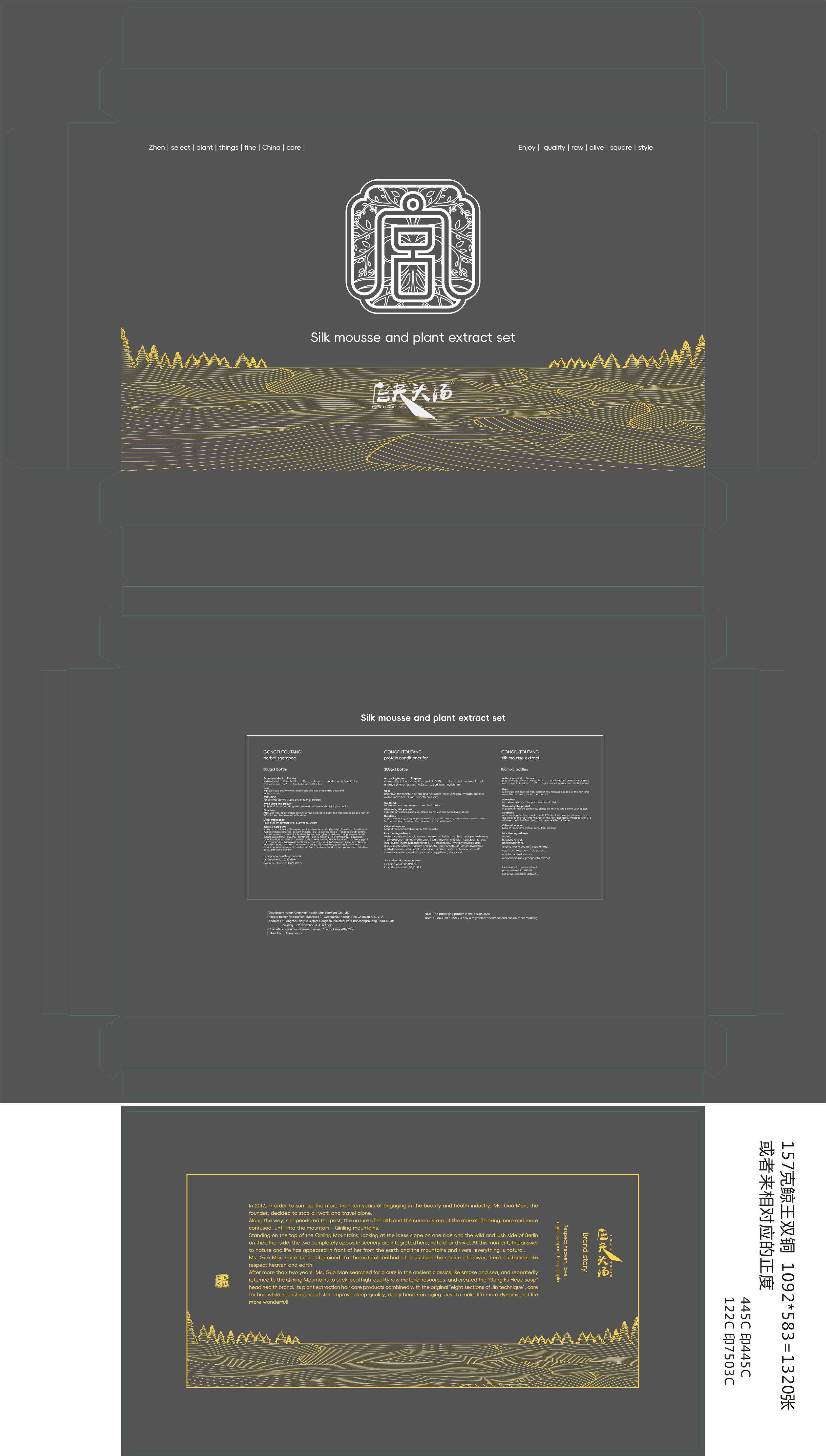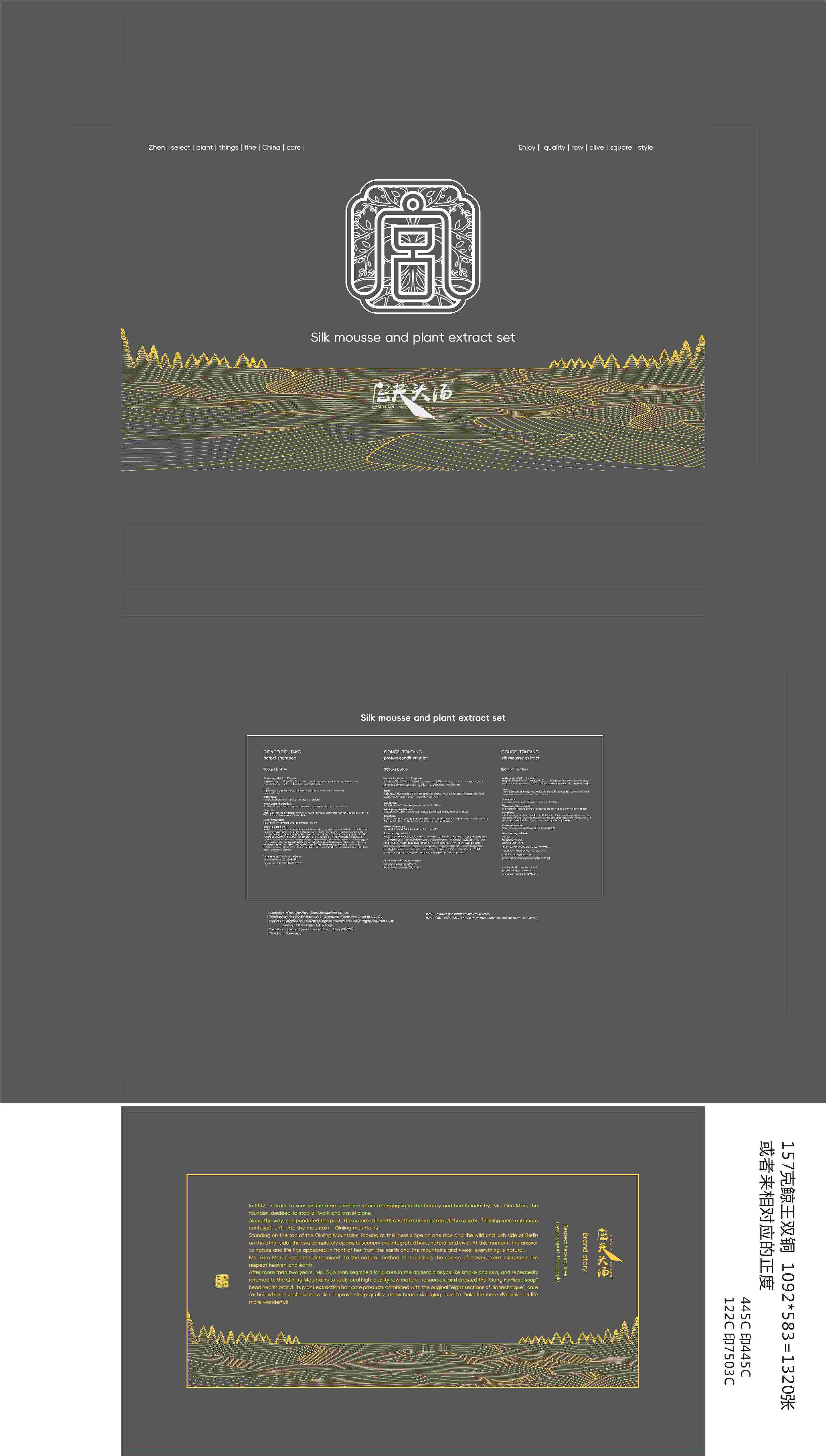 DRUG LABEL: GONGFUTOUYANG silk mousse extract
NDC: 84286-003 | Form: LIQUID
Manufacturer: Henan Chanman Health Management Co., Ltd
Category: otc | Type: HUMAN OTC DRUG LABEL
Date: 20240506

ACTIVE INGREDIENTS: ANGELICA SINENSIS ROOT 0.5 g/100 mL; PLATYCLADUS ORIENTALIS LEAF 0.7 g/100 mL
INACTIVE INGREDIENTS: WATER; SOYBEAN; ECLIPTA PROSTRATA LEAF; TABASCO PEPPER; PHENOXYETHANOL; BUTYLENE GLYCOL; REHMANNIA GLUTINOSA ROOT

84286-001 002 003

Active Ingredient

GONGFUTOUYANG herbal shampoo

sodium laureth sulfate 12.6% cocamide dea 1.7%

GONGFUTOUYANG protein conditioner for

simmondsia chinensis(jojoba)seed oil 0.2% angelica sinensis extract 0.2%

GONGFUTOUYANG silk mousse extract

polygonum multiflorum extract 0.7% morus nigra fruit extract 0.5%

Purpose

lean scalp, remove dandruff and relieve itching，moisturize and soften hair

Use

Improve scalp environment, clean scalp and hair oil and dirt, clean and
moisturize hair.

Warnings

For extemal use only. Keep out ofreach of children

Do not use

if discomfort occurs during use, please do not use and consuit vour doctor

When Using

Improve scalp environment, clean scalp and hair oil and dirt, clean and moisturize hair.if discomfort occurs during use, please do not use and consuit vour doctor

Stop Use

if discomfort occurs during use, please do not use and consuit vour doctor

Ask Doctor

if discomfort occurs during use, please do not use and consuit vour doctor

Keep Oot Of Reach Of Children

Keep out ofreach of children

Directions

After wet hair, apply proper amount of this product to clean and massage scalp and hair for2-5 minutes, then rinse off with water

Other information

Keep at room temperature, away from sunlight

Inactive ingredients

GONGFUTOUYANG herbal shampoo

water
cocamidopropyl betaine
sodium chloride
caprylyl/capryl glucoside
dimethicone
hydrogenated castor oil
sodium chloride
c12-18 alkyl alucoside
sodium laureth sulfate
cocamide mea
methyichloroisothiazolinone
methylisothiazolinone
magnesium chloride
magnesium nitrate
glycerin
aureth-23
c12-15 pareth-3，polyaminopropyl biguanide
amodimethicone,
steartrimonium chloride
isolaureth-6
dmdm hydantoin
butylene glycol
1,2-hexanediol
hydroxyacetophenone
caramel
guar hydroxypropyltrimonium chloride
methylparaben
allantoin
behenamidopropyl dimethylamine
panthenol
citric acid
aroma
polyquaternium-10
sodium acetate
sodium chloride
isopropyl alcohol
disodiumedta
piroctone olamine

GONGFUTOUYANG protein conditioner for

water
cetearyl alcohol
ceteartrimonium chloride
alcohol
cyclopentasiloxanedimethicone
dimethicone
amodimethicone
steartrimonium chloride
isolaureth-6
buty-lene glycol
hydroxyacetophenone
1,2-hexanediol
hydroxyethylcellulose
disodium phosphate
sodium phosphate
polysorbate 60
dmdm hydantoin
methylparaben
citric acid
squalane
ci 19140
sodium chloride
ci 15985
camellia japonica seed oil
macrocystis pyrifera (kelp) protein

GONGFUTOUYANG silk mousse extract

water
butylene glycol
phenoxyethanol
glycine max (soybean) seed extract
capsicum frutescens fruit extract
eclipta prostrata extract
rehmanniae radix praeparata extract